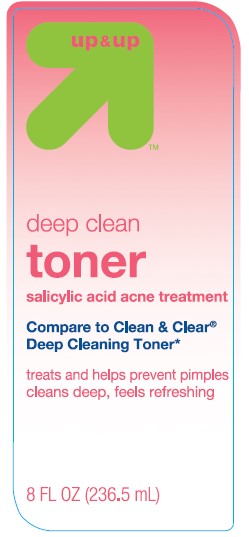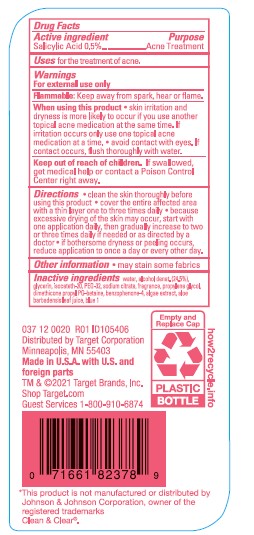 DRUG LABEL: Up and Up
NDC: 11673-936 | Form: LIQUID
Manufacturer: TARGET CORPORATION
Category: otc | Type: HUMAN OTC DRUG LABEL
Date: 20241014

ACTIVE INGREDIENTS: SALICYLIC ACID 5 mg/1 mL
INACTIVE INGREDIENTS: TRISODIUM CITRATE DIHYDRATE; ALCOHOL; WATER; GLYCERIN; FD&C BLUE NO. 1; POLYETHYLENE GLYCOL 1600; PHYMATOLITHON CALCAREUM; PROPYLENE GLYCOL; SULISOBENZONE; ISOCETETH-20; ALOE VERA LEAF; DIMETHICONE PROPYL PG-BETAINE

Up & Up Deep Clean Toner

Active ingredient

Salicylic Acid 0.5%

Purpose

Acne Treatment

Uses

- for the treatment of acne.

Warnings

For external use only

When using this product

• skin irritation and dryness is more likely to occur if you use another topical acne medication at the same time. If irritation occurs only use one topical acne medication at a time. • avoid contact with eyes. If contact occurs, flush thoroughly with water.

Keep out of reach of children.

If swallowed, get medical help or contact a Poison Control Center right away.

Directions

• clean the skin thoroughly before using this product • cover the entire affected area with a thin layer one to three times daily • because excessive drying of the skin may occur, start with one application daily, then gradually increase to two or three times daily if needed or as directed by doctor • if bothersome dryness or peeling occurs, reduce application to once a day or every other day.

Other information

• may stain some fabric

Inactive ingredients

water, alcohol denat. (24.5 %), glycerin, isoceteth-20, PEG-32, sodium citrate, fragrance, propylene glycol, dimethicone propyl PG-betaine, benozphenone-4, algae extract, aloe barbadenis leaf juice, blue 1

PACKAGE LABEL

Up & Up Deep Clean Toner

8 FL OZ (236.5 mL)

NDC 11676-936-11